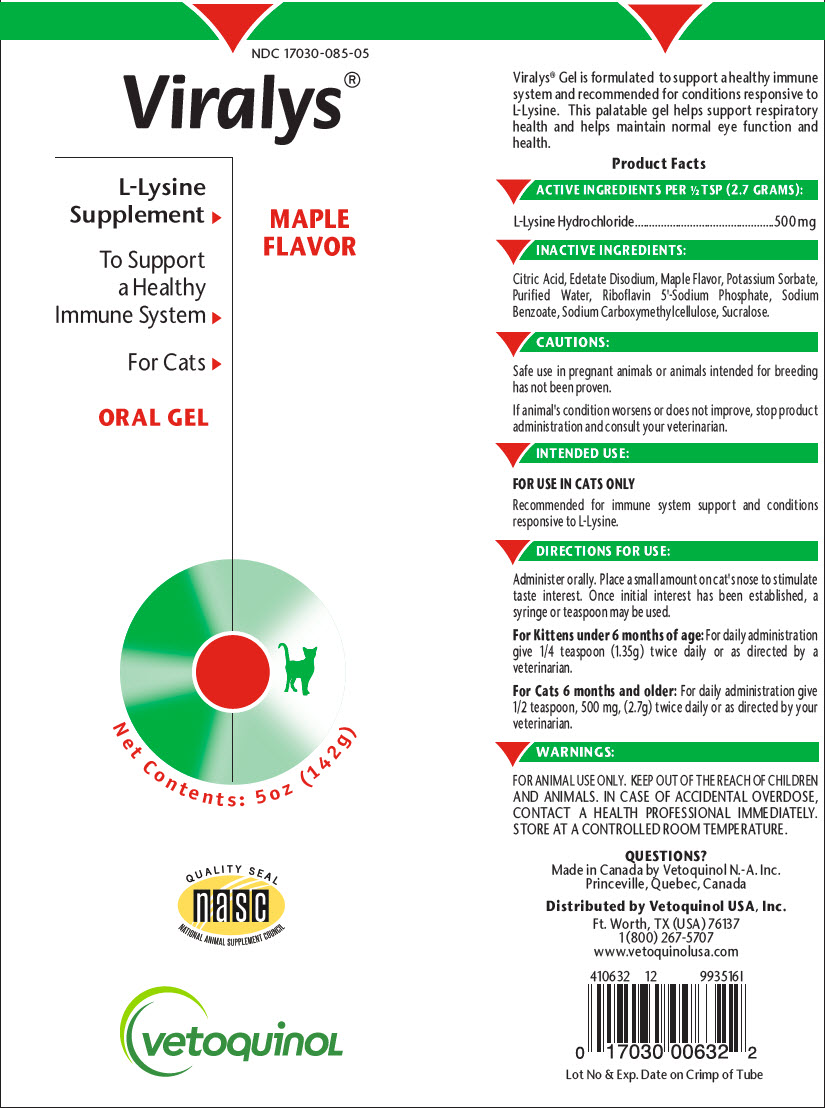 DRUG LABEL: VIRALYS
NDC: 17030-085 | Form: GEL
Manufacturer: Vetoquinol USA, Inc.
Category: animal | Type: OTC ANIMAL DRUG LABEL
Date: 20200213

ACTIVE INGREDIENTS: LYSINE HYDROCHLORIDE 185.18 mg/2.7 g
INACTIVE INGREDIENTS: CITRIC ACID MONOHYDRATE; EDETATE DISODIUM; POTASSIUM SORBATE; WATER; RIBOFLAVIN 5'-PHOSPHATE SODIUM ANHYDROUS; SODIUM BENZOATE; CARBOXYMETHYLCELLULOSE SODIUM, UNSPECIFIED FORM; SUCRALOSE

VIRALYS®

VETERINARY INDICATIONS

Viralys® Gel is formulated to support a healthy immune system and recommended for conditions responsive to L-Lysine. This palatable gel helps support respiratory health and helps maintain normal eye function and health.

Product Facts

DESCRIPTION

ACTIVE INGREDIENTS PER ½ TSP (2.7 GRAMS):

L-Lysine Hydrochloride | 500 mg

INACTIVE INGREDIENTS:

Citric Acid, Edetate Disodium, Maple Flavor, Potassium Sorbate, Purified Water, Riboflavin 5'-Sodium Phosphate, Sodium Benzoate, Sodium Carboxymethylcellulose, Sucralose.

PRECAUTIONS

CAUTIONS:

Safe use in pregnant animals or animals intended for breeding has not been proven.

If animal's condition worsens or does not improve, stop product administration and consult your veterinarian.

INDICATIONS AND USAGE

INTENDED USE:

FOR USE IN CATS ONLY

Recommended for immune system support and conditions responsive to L-Lysine.

DOSAGE AND ADMINISTRATION

DIRECTIONS FOR USE:

Administer orally. Place a small amount on cat's nose to stimulate taste interest. Once initial interest has been established, a syringe or teaspoon may be used.

For Kittens under 6 months of age: For daily administration give 1/4 teaspoon (1.35g) twice daily or as directed by a veterinarian.

For Cats 6 months and older: For daily administration give 1/2 teaspoon, 500 mg, (2.7g) twice daily or as directed by your veterinarian.

WARNINGS:

FOR ANIMAL USE ONLY. KEEP OUT OF THE REACH OF CHILDREN AND ANIMALS. IN CASE OF ACCIDENTAL OVERDOSE, CONTACT A HEALTH PROFESSIONAL IMMEDIATELY. STORE AT A CONTROLLED ROOM TEMPERATURE.

QUESTIONS?

Made in Canada by Vetoquinol N.-A. Inc.
Princeville, Quebec, Canada

Distributed by Vetoquinol USA, Inc.
Ft. Worth, TX (USA) 76137
1 (800) 267-5707
www.vetoquinolusa.com

Lot No & Exp. Date on Crimp of Tube

PRINCIPAL DISPLAY PANEL - 142 g Tube Label

NDC 17030-085-05

Viralys®

L-Lysine
Supplement ⏵

To Support
a Healthy
Immune System ⏵

For Cats ⏵

ORAL GEL

MAPLE
FLAVOR

Net Contents: 5 oz (142g)

QUALITY SEAL
nasc
NATIONAL ANIMAL SUPPLEMENT COUNCIL

vetoquinol